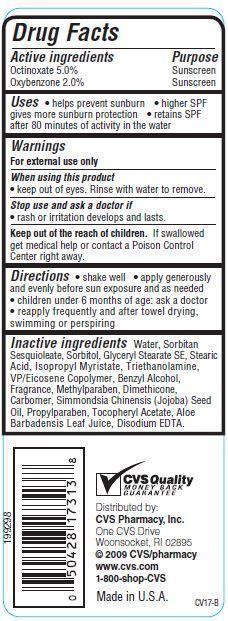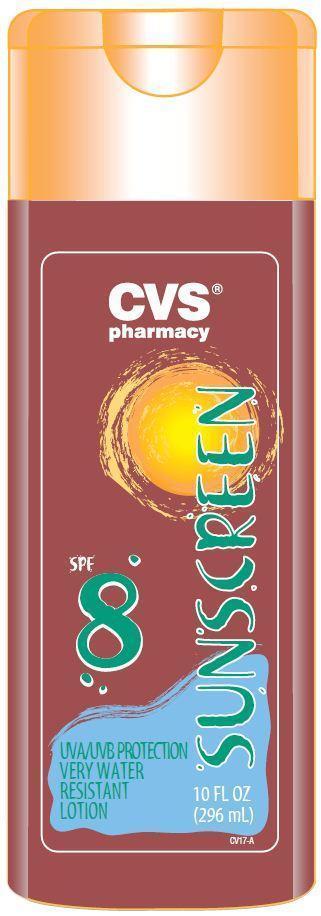 DRUG LABEL: CVS SPF 8
NDC: 59779-000 | Form: LOTION
Manufacturer: CVS Pharmacy
Category: otc | Type: HUMAN OTC DRUG LABEL
Date: 20121211

ACTIVE INGREDIENTS: OCTINOXATE 5 g/100 g; OXYBENZONE 2 g/100 g
INACTIVE INGREDIENTS: EDETATE DISODIUM; ALOE VERA LEAF; WATER; SORBITAN SESQUIOLEATE; SORBITOL; GLYCERYL STEARATE SE; STEARIC ACID; ISOPROPYL MYRISTATE; TROLAMINE; BENZYL ALCOHOL; METHYLPARABEN; DIMETHICONE; JOJOBA OIL; PROPYLPARABEN; .ALPHA.-TOCOPHEROL ACETATE

Drug Facts

Active ingredients

Octinoxate 5.0%
Oxybenzone 2.0%

Purpose

Sunscreen

Uses

- helps prevent sunburn
- higher SPF gives more sunburn protection
- retains SPF after 80 minutes of activity in water

Warnings

For external use only

When using this product

- keep out of eyes. Rinse with water to remove.

Stop use and ask a doctor if

- rash or irritation develops and lasts.

Keep out of the reach of children.
If swallowed get medical help or contact a Poison Control Center right away.

Directions

- shake well
- apply generously and evenly before sun exposure and as needed
- children under 6 months of age: ask a doctor
- reapply frequently and after towel drying, swimming or perspiring

Inactive ingredients

Water, Sorbitan Sesquioleate, Sorbitol, Glyceryl Stearate SE, Stearic Acid, Isopropyl Myristate, Triethanolamine, VP/Eicosene Copolymer, Benzyl Alcohol, Fragrance, Methylparaben, Dimethicone, Carbomer, Simmondsia Chinensis (Jojoba) Seed Oil, Propylparaben, Tocopheryl Acetate, Aloe Barbadensis Leaf Juice, Disodium EDTA.

Principal Display Panel

CVS
pharmacy
SUNSCREEN
SPF 8
UVA/UVB Protection
VERY WATER
RESISTANT
LOTION
10 FL OZ (296 mL)